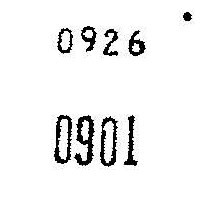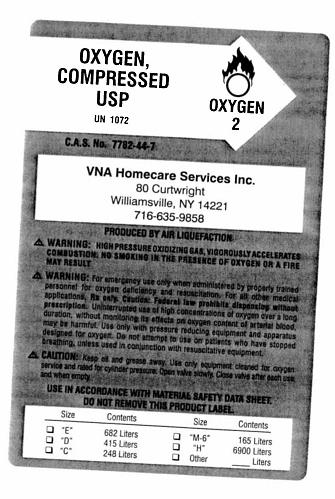 DRUG LABEL: Oxygen
NDC: 67942-2100 | Form: GAS
Manufacturer: VNA Homecare Services
Category: prescription | Type: HUMAN PRESCRIPTION DRUG LABEL
Date: 20090925

ACTIVE INGREDIENTS: Oxygen 99 L/100 L

Oxygen